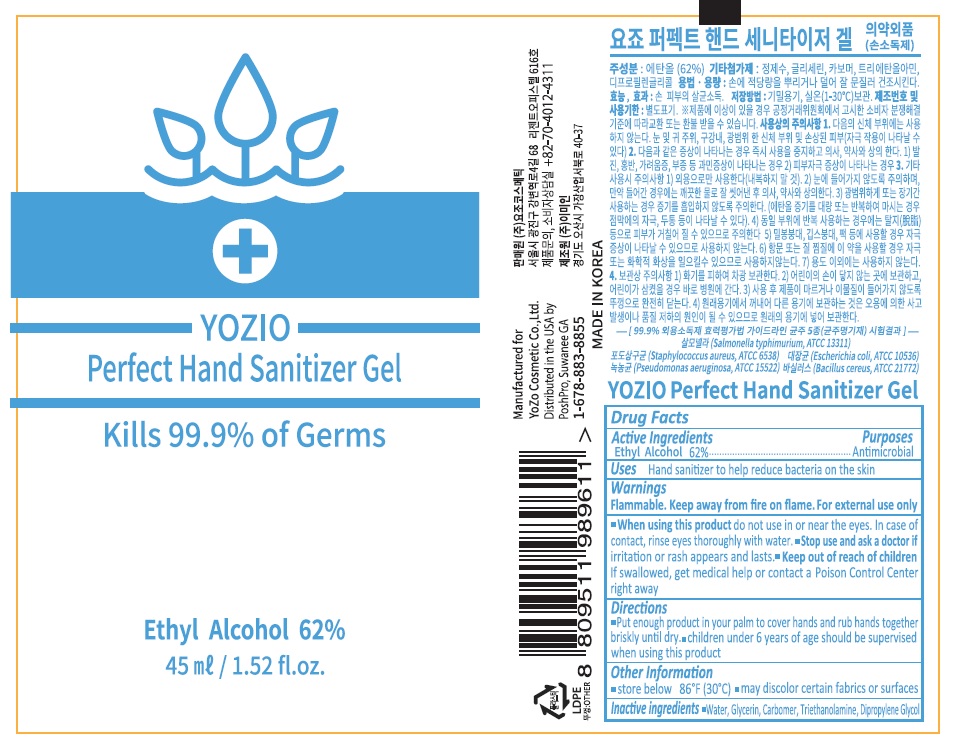 DRUG LABEL: YOZIO Perfect Hand Sanitizer gel
NDC: 77718-001 | Form: GEL
Manufacturer: YOZO COSMETIC Co.,Ltd
Category: otc | Type: HUMAN OTC DRUG LABEL
Date: 20200513

ACTIVE INGREDIENTS: ALCOHOL 0.62 g/1 mL
INACTIVE INGREDIENTS: WATER; GLYCERIN; DIPROPYLENE GLYCOL; CARBOMER HOMOPOLYMER, UNSPECIFIED TYPE; TROLAMINE

77718-001_YOZIO Perfect Hand Sanitizer Gel

Active ingredient

Ethyl alcohol 62%

Purpose

Antimicrobial

Use

- Hand sanitizer to help reduce bacteria on the skin

Warnings

Flammable. Keep away from fire or flame.

For external use only

When using this product do not use in or near the eyes. In case of contact, rinse eyes thoroughly with water.

Stop use and ask a doctor if irritation or rash appears and lasts

Keep out of reach of children. If swallowed, get medical help or contact a Poison Control Center right away.

Directions

- Put nough produt in your palm to cover hands and rub hands together briskly until dry.
- Children under 6 years of age should be supervised when using this product

Other information

- Store below 86°F (30°C)
- May discolor certain fabrics or surfaces

Inactive ingredients

Water, Glycerin, Carbomer, Triethanolamine, Dipropylene Glycol